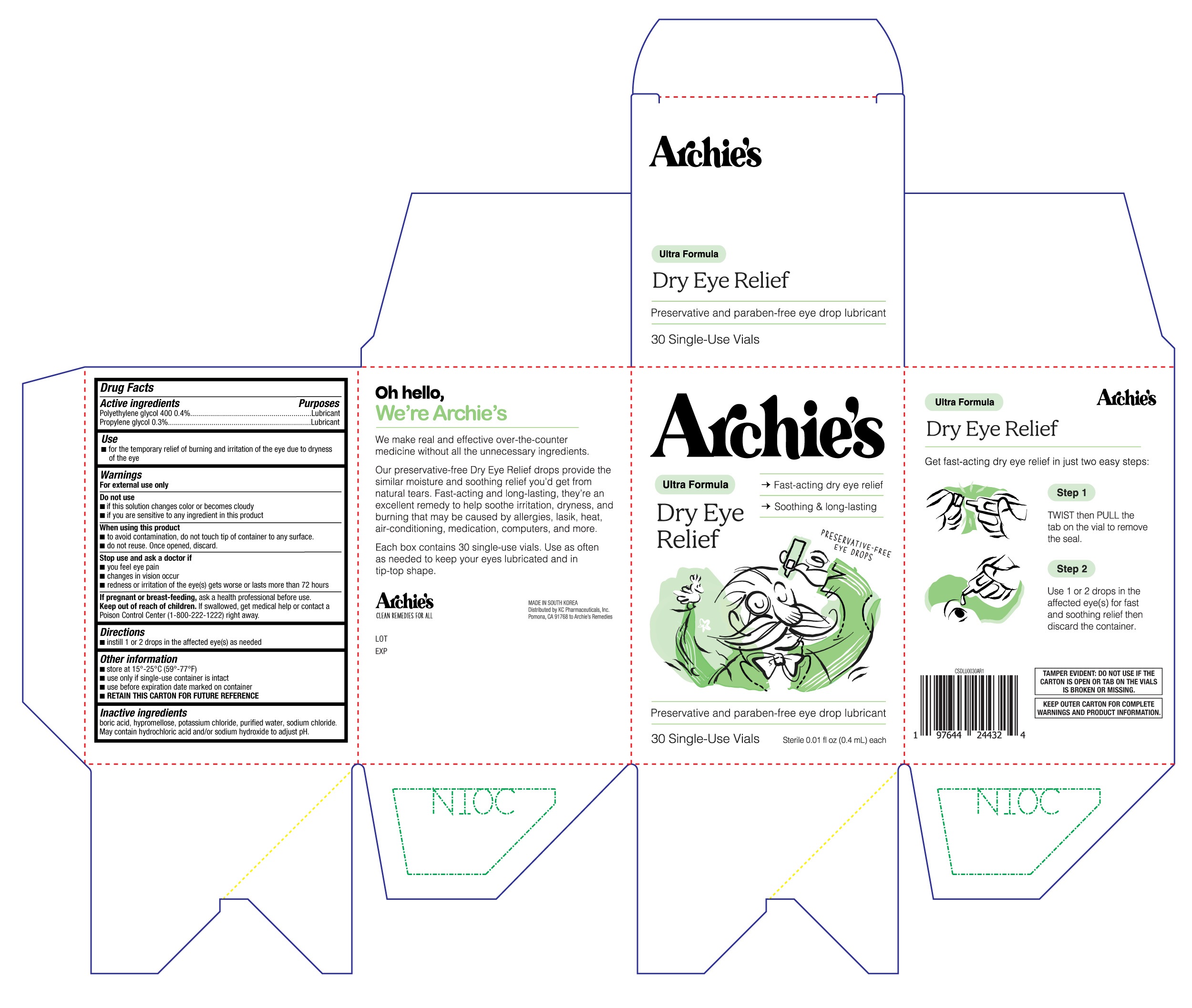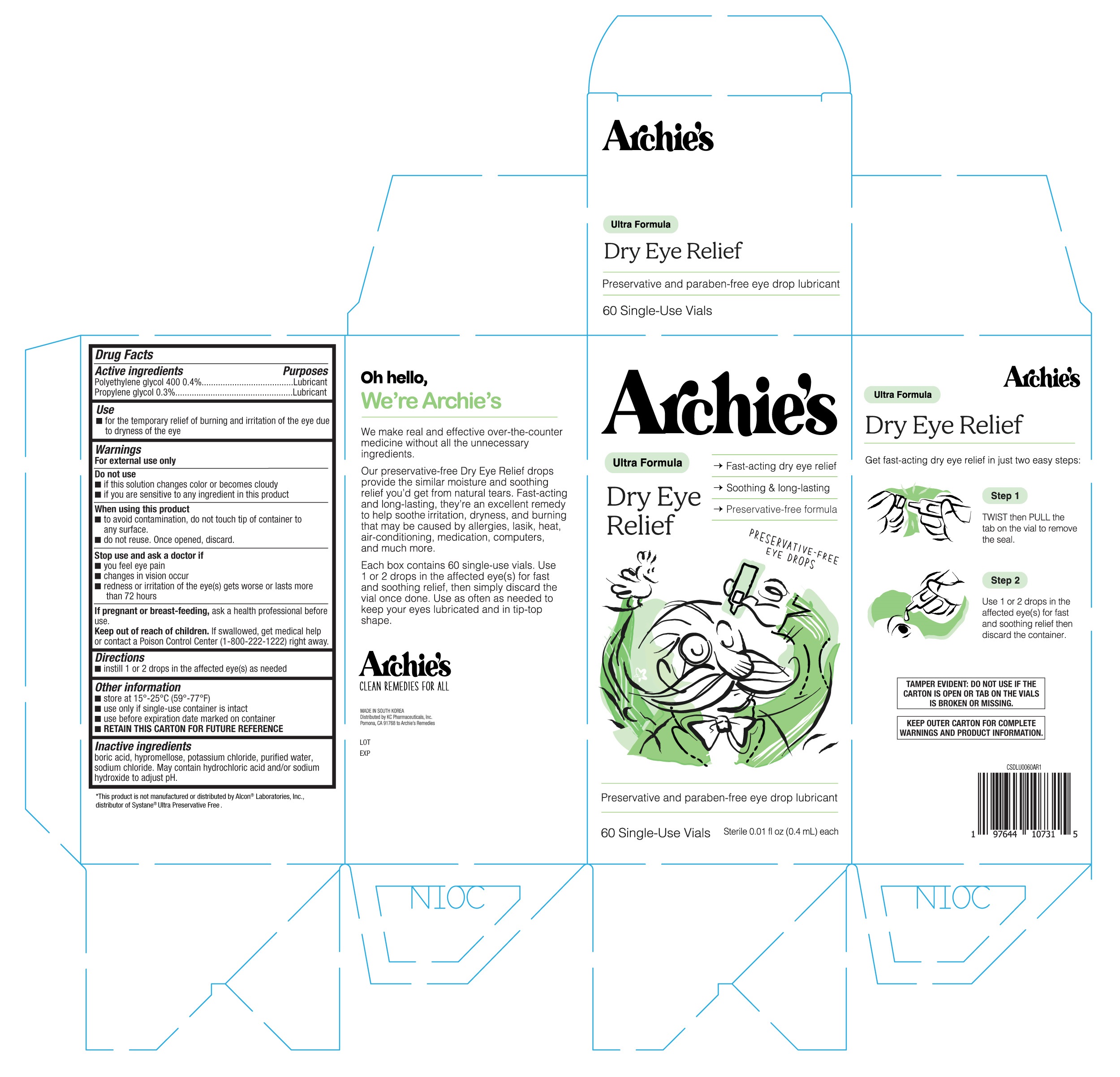 DRUG LABEL: Archies Dry Eye Relief
NDC: 83737-001 | Form: SOLUTION/ DROPS
Manufacturer: Archie's Remedies
Category: otc | Type: HUMAN OTC DRUG LABEL
Date: 20251230

ACTIVE INGREDIENTS: POLYETHYLENE GLYCOL 400 0.4 g/100 mL; PROPYLENE GLYCOL 0.3 g/100 mL
INACTIVE INGREDIENTS: POTASSIUM CHLORIDE; WATER; HYDROCHLORIC ACID; SODIUM CHLORIDE; HYPROMELLOSE, UNSPECIFIED; SODIUM HYDROXIDE; BORIC ACID

Archie's Dry Eye Relief 30ct & 60ct (PLD)

Active ingredients

Polyethylene glycol 400 0.4%

Propylene glycol 0.3%

Purposes

Lubricant

Lubricant

Use

- for the temporary relief of burning and irritation of the eye due to dryness of the eye

Warnings

For external use only

Do not use

- if this solution changes color or becomes cloudy
- if you are sensitive to any ingredient in this product

When using this product

- to avoid contamination, do not touch tip of container to any surface.
- do not reuse. Once opened, discard.

Stop use and ask a doctor if

- you feel eye pain
- changes in vision occur
- redness or irritation of the eye(s) gets worse or lasts more than 72 hours

If pregnant or breast-feeding,

ask a health professional before use.

Keep out of reach of children.

If swallowed, get medical help or contact a Poison Control Center (1-800-222-1222) right away.

Directions

- instill 1 or 2 drops in the affected eye(s) as needed

Other information

- store at 15°-25°C (59°-77°F)
- use only if single-use container is intact
- use before expiration date marked on container
- RETAIN THIS CARTON FOR FUTURE REFERENCE

Inactive ingredients

boric acid, hypromellose, potassium chloride, purified water, sodium chloride. May contain hydrochloric acid and/or sodium hydroxide to adjust pH.